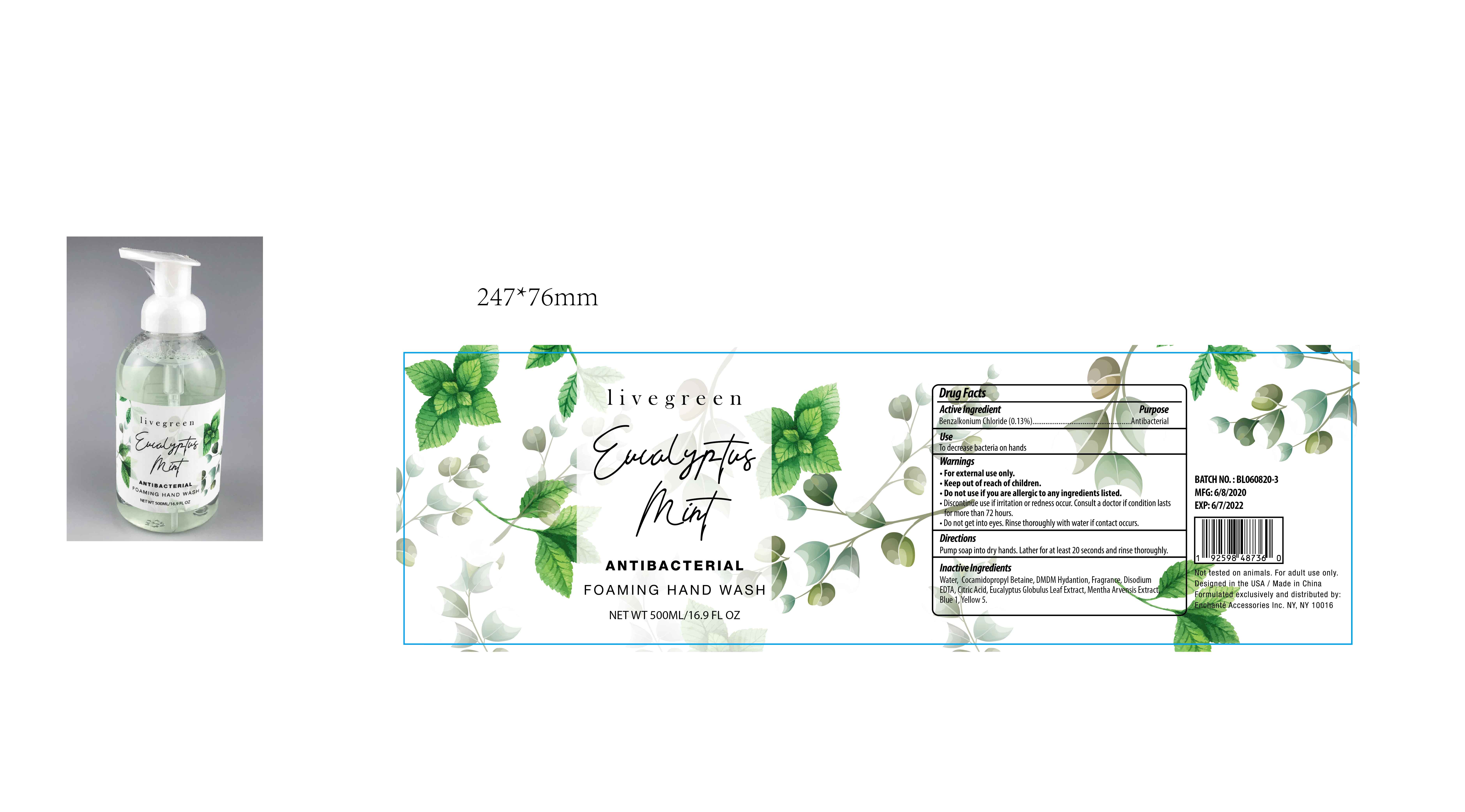 DRUG LABEL: livegreen Eucalyptus Mint ANTIBACTERIAL FOAMING HAND WASH
NDC: 50563-233 | Form: SOLUTION
Manufacturer: ENCHANTE ACCESSORIES INC.
Category: otc | Type: HUMAN OTC DRUG LABEL
Date: 20200630

ACTIVE INGREDIENTS: BENZALKONIUM CHLORIDE 0.13 g/100 mL
INACTIVE INGREDIENTS: COCAMIDOPROPYL BETAINE; DMDM HYDANTOIN; DISODIUM HEDTA; CITRIC ACID MONOHYDRATE; EUCALYPTUS GLOBULUS LEAF; WATER; FD&C YELLOW NO. 5; FD&C BLUE NO. 1; MENTHA ARVENSIS WHOLE

G0ABHW03

Active Ingredient

Benzalkonium Chloride 0.13%

Purpose

Antibacterial

Use

■ To decrease bacteria on hands

WARNINGS

For external use only

Do not use if you are allergic to any ingredients listed

Discontinue use if irritation or redness occur. Consult a doctor if condition lasts for more than 72 hours

Do not get into eyes. Rinse thoroughly with water if contact occurs

keep out of reach of children

Directions

Pump soap into dry hands. Lather for at least 20 seconds and rinse thoroughly

Inactive ingredients

Water, Cocamidopropyl Betaine, DMDM Hydantoin, Fragrance, Disodium EDTA, Citric Acid, Eucalyptus Globulus Leaf Extract, Mentha Arvensis
Extract, Yellow 5, Blue 1